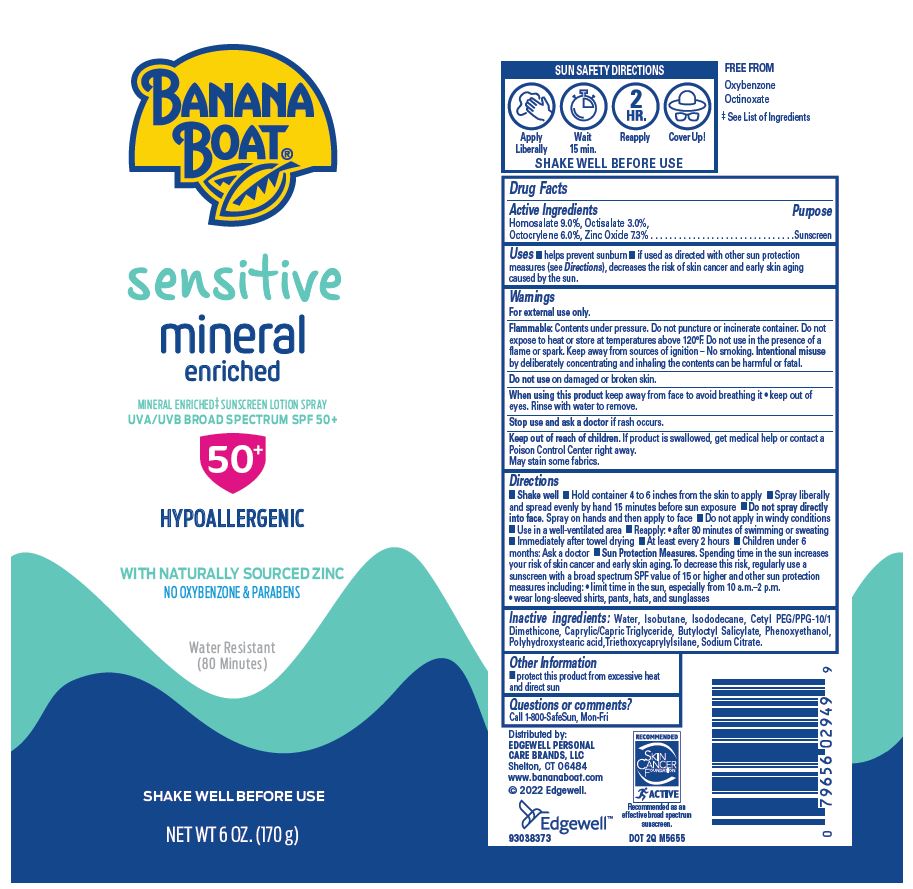 DRUG LABEL: Banana Boat simply protect sensitive MINERAL ENRICHED SUNSCREEN UVA/UVB BROAD SPECTRUM SPF 50
NDC: 63354-261 | Form: SPRAY
Manufacturer: Edgewell Personal Care Brands, LLC
Category: otc | Type: HUMAN OTC DRUG LABEL
Date: 20241125

ACTIVE INGREDIENTS: ZINC OXIDE 7.3 g/100 g; HOMOSALATE 9 g/100 g; OCTISALATE 3 g/100 g; OCTOCRYLENE 6 g/100 g
INACTIVE INGREDIENTS: WATER; ISODODECANE; ANHYDROUS TRISODIUM CITRATE; TRIETHOXYCAPRYLYLSILANE; POLYHYDROXYSTEARIC ACID (2300 MW); PHENOXYETHANOL; BUTYLOCTYL SALICYLATE; CETYL PEG/PPG-10/1 DIMETHICONE (HLB 2); ISOBUTANE; MEDIUM-CHAIN TRIGLYCERIDES

Active Ingredients

Homosalate 9.0%, Octisalate 3.0%, Octocrylene 6.0%, Zinc Oxide 7.3%

Purpose

Sunscreen

Uses

• helps prevent sunburn • if used as directed with other sun protection measures (see Directions), decreases the risk of skin cancer and early skin aging caused by the sun.

Warnings

For external use only.

May stain some fabrics.

Flammable

Contents under pressure. Do not puncture or incinerate container. Do not expose to heat or store at temperatures above 120°F. Do not use in the presence of a flame or spark. Keep away from sources of ignition - No smoking. Intentional misuse by deliberately concentrating and inhaling the contents can be harmful or fatal.

Do not use

on damaged or broken skin.

When using this product

keep away from face to avoid breathing it • keep out of eyes. Rinse with water to removed.

Stop use and ask a doctor

if rash occurs.

Keep out of reach of children.

If product is swallowed, get medical help or contact a Poison Control Center right away.

Directions

• Shake well • Hold container 4 to 6 inches from the skin to apply • Spray liberally and spread evenly by hand 15 minutes before sun exposure • Do not spray directly into face. Spray on hands and then apply to face • Do not apply in windy conditions • Use in well-ventilated area • Reapply:• after 80 minutes of swimming or sweating • Immediately after towel drying • At least every 2 hours • Children under 6 months: Ask a doctor • Sun Protection Measures. Spending time in the sun increases your risk of skin cancer and early skin aging. To decrease this risk, regularly use a sunscreen with a broad spectrum SPF value of 15 or higher and other sun protection measures including:• limit time in the sun, especially from 10 a.m.-2 p.m. • wear long-sleeved shirts, pants, hats, and sunglasses

Inactive ingredients

Water, Isobutane, Isododecane, Cetyl PEG/PPG-10/1 Dimethicone, Caprylic/Capric Triglyceride, Butyloctyl Salicylate, Phenoxyethanol, Polyhydroxystearic acid, Triethoxycaprylylsilane, Sodium Citrate.

Other information

protect this product from excessive heat and direct sun

Questions or comments?

Call 1-800-SafeSun, Mon-Fri

Principal Display Panel

BANANA
BOAT®
sensitive
mineral
enriched
MINERAL ENRICHED SUNSCREEN LOTION SPRAY
UVA/UVB BROAD SPECTRUM SPF 50+
50+
HYPOALLERGENIC
WITH NATURALLY SOURCED ZINC
NO OXYBENZONE & PARABENS
Water Resistant
(80 Minutes)
SHAKE WELL BEFORE USE
NET WT 6 OZ. (170 g)